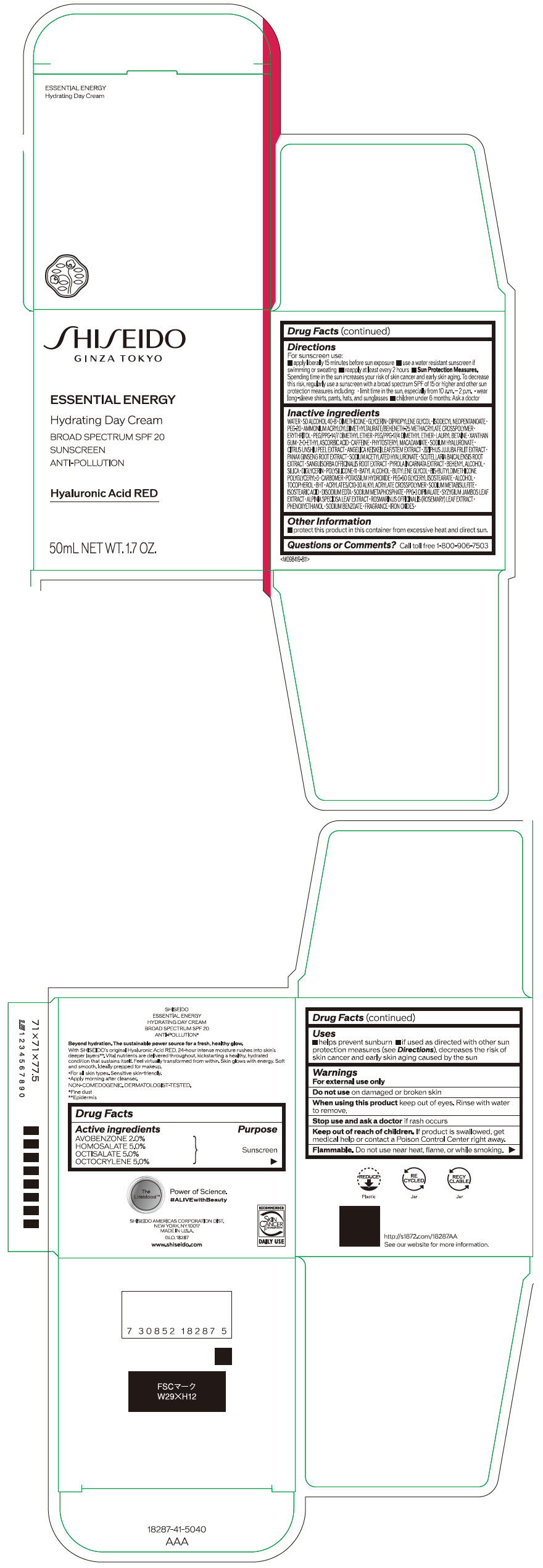 DRUG LABEL: SHISEIDO ESSENTIAL ENERGY HYDRATING DAY
NDC: 58411-656 | Form: EMULSION
Manufacturer: SHISEIDO AMERICAS CORPORATION
Category: otc | Type: HUMAN OTC DRUG LABEL
Date: 20260217

ACTIVE INGREDIENTS: HOMOSALATE 2.53 g/50 mL; OCTOCRYLENE 2.53 g/50 mL; OCTISALATE 2.53 g/50 mL; AVOBENZONE 1.012 g/50 mL
INACTIVE INGREDIENTS: WATER; DIMETHICONE; GLYCERIN; DIPROPYLENE GLYCOL; ISODECYL NEOPENTANOATE; POLYETHYLENE GLYCOL 1000; PHENOXYETHANOL; DOCOSANOL; SILICON DIOXIDE; DIGLYCERIN; DIMETHICONE/VINYL DIMETHICONE CROSSPOLYMER (SOFT PARTICLE); AMMONIUM ACRYLOYLDIMETHYLTAURATE/BEHENETH-25 METHACRYLATE CROSSPOLYMER (52000 MPA.S); BATILOL; BUTYLENE GLYCOL; CARBOMER HOMOPOLYMER, UNSPECIFIED TYPE; POTASSIUM HYDROXIDE; PEG/PPG-14/7 DIMETHYL ETHER; PEG/PPG-17/4 DIMETHYL ETHER; ERYTHRITOL; PEG-60 GLYCERYL ISOSTEARATE; LAURYL BETAINE; ALCOHOL; .ALPHA.-TOCOPHEROL; 2-O-ETHYL ASCORBIC ACID; BUTYLATED HYDROXYTOLUENE; XANTHAN GUM; CARBOMER INTERPOLYMER TYPE A (ALLYL SUCROSE CROSSLINKED); SODIUM METABISULFITE; CAFFEINE; ISOSTEARIC ACID; SODIUM POLYMETAPHOSPHATE; EDETATE DISODIUM; PHYTOSTERYL MACADAMIATE; FERRIC OXIDE RED; FERRIC OXIDE YELLOW; FERROSOFERRIC OXIDE; HYALURONATE SODIUM; TANGERINE PEEL; ANGELICA KEISKEI TOP; JUJUBE FRUIT; ASIAN GINSENG; SODIUM ACETYLATED HYALURONATE; SCUTELLARIA BAICALENSIS ROOT; SYZYGIUM JAMBOS LEAF; ALPINIA ZERUMBET LEAF; SODIUM BENZOATE; ROSEMARY; SANGUISORBA OFFICINALIS ROOT

SHISEIDO ESSENTIAL ENERGY HYDRATING DAY CREAM

Drug Facts

ACTIVE INGREDIENT

Active ingredients | Purpose
AVOBENZONE 2.0% | Sunscreen
HOMOSALATE 5.0% | Sunscreen
OCTISALATE 5.0% | Sunscreen
OCTOCRYLENE 5.0% | Sunscreen

Uses

- helps prevent sunburn
- if used as directed with other sun protection measures (see Directions), decreases the risk of skin cancer and early skin aging caused by the sun

Warnings

For external use only

Do not use on damaged or broken skin

WHEN USING

When using this productkeep out of eyes. Rinse with water to remove.

Stop use and ask a doctorif rash occurs.

Keep out of reach of children.If product is swallowed, get medical help or contact a Poison Control Center right away.

Flammable.Do not use near heat, flame. or while smoking

Directions

For sunscreen use:

- apply liberally 15 minutes before sun exposure
- use a water resistant sunscreen if swimming or sweating
- reapply at least every two hours
- Sun Protection Measures.
  Spending time in the sun increases your risk of skin cancer and early skin aging. To decrease this risk, regularly use a sunscreen with a broad spectrum SPF of 15 or higher and other sun protection measures including:
  - limit time in the sun, especially from 10 a.m. – 2 p.m.
  - wear long-sleeve shirts, pants, hats, and sunglasses
- children under 6 months: Ask a doctor

Inactive Ingredients

WATER ∙ SD ALCOHOL 40-B ∙ DIMETHICONE ∙ GLYCERIN ∙ DIPROPYLENE GLYCOL ∙ ISODECYL NEOPENTANOATE ∙ PEG-20 ∙ AMMONIUM ACRYLOYLDIMETHYLTAURATE/BEHENETH-25 METHACRYLATE CROSSPOLYMER ∙ ERYTHRITOL ∙ PEG/PPG-14/7 DIMETHYL ETHER ∙ PEG/PPG-17/4 DIMETHYL ETHER ∙ LAURYL BETAINE ∙ XANTHAN GUM ∙ 2-O-ETHYL ASCORBIC ACID ∙ CAFFEINE ∙ PHYTOSTERYL MACADAMIATE ∙ SODIUM HYALURONATE ∙ CITRUS UNSHIU PEEL EXTRACT ∙ ANGELICA KEISKEI LEAF/STEM EXTRACT ∙ ZIZIPHUS JUJUBA FRUIT EXTRACT ∙ PANAX GINSENG ROOT EXTRACT ∙ SODIUM ACETYLATED HYALURONATE ∙ SCUTELLARIA BAICALENSIS ROOT EXTRACT ∙ SANGUISORBA OFFICINALIS ROOT EXTRACT ∙ PYROLA INCARNATA EXTRACT ∙ BEHENYL ALCOHOL ∙ SILICA ∙ DIGLYCERIN ∙ POLYSILICONE-11 ∙ BATYL ALCOHOL ∙ BUTYLENE GLYCOL ∙ BIS-BUTYLDIMETHICONE POLYGLYCERYL-3 ∙ CARBOMER ∙ POTASSIUM HYDROXIDE ∙ PEG-60 GLYCERYL ISOSTEARATE ∙ ALCOHOL ∙ TOCOPHEROL ∙ BHT ∙ ACRYLATES/C10-30 ALKYL ACRYLATE CROSSPOLYMER ∙ SODIUM METABISULFITE ∙ ISOSTEARIC ACID ∙ DISODIUM EDTA ∙ SODIUM METAPHOSPHATE ∙ PPG-3 DIPIVALATE ∙ SYZYGIUM JAMBOS LEAF EXTRACT ∙ ALPINIA SPECIOSA LEAF EXTRACT ∙ ROSMARINUS OFFICINALIS (ROSEMARY) LEAF EXTRACT ∙ PHENOXYETHANOL ∙ SODIUM BENZOATE ∙ FRAGRANCE ∙ IRON OXIDES

Other information

Protect this product in this container from excessive heat and direct sun.

Questions or comments?

Call toll free 1-800-906-7503

PRINCIPAL DISPLAY PANEL - 50 mL Tube Carton

SHISEIDO
GINZA TOKYO

ESSENTIAL ENERGY

Hydrating Day Cream
BROAD SPECTRUM SPF 20
SUNSCREEN
ANTI-POLLUTION

Hyaluronic Acid RED

50mL NET WT. 1.7 OZ.